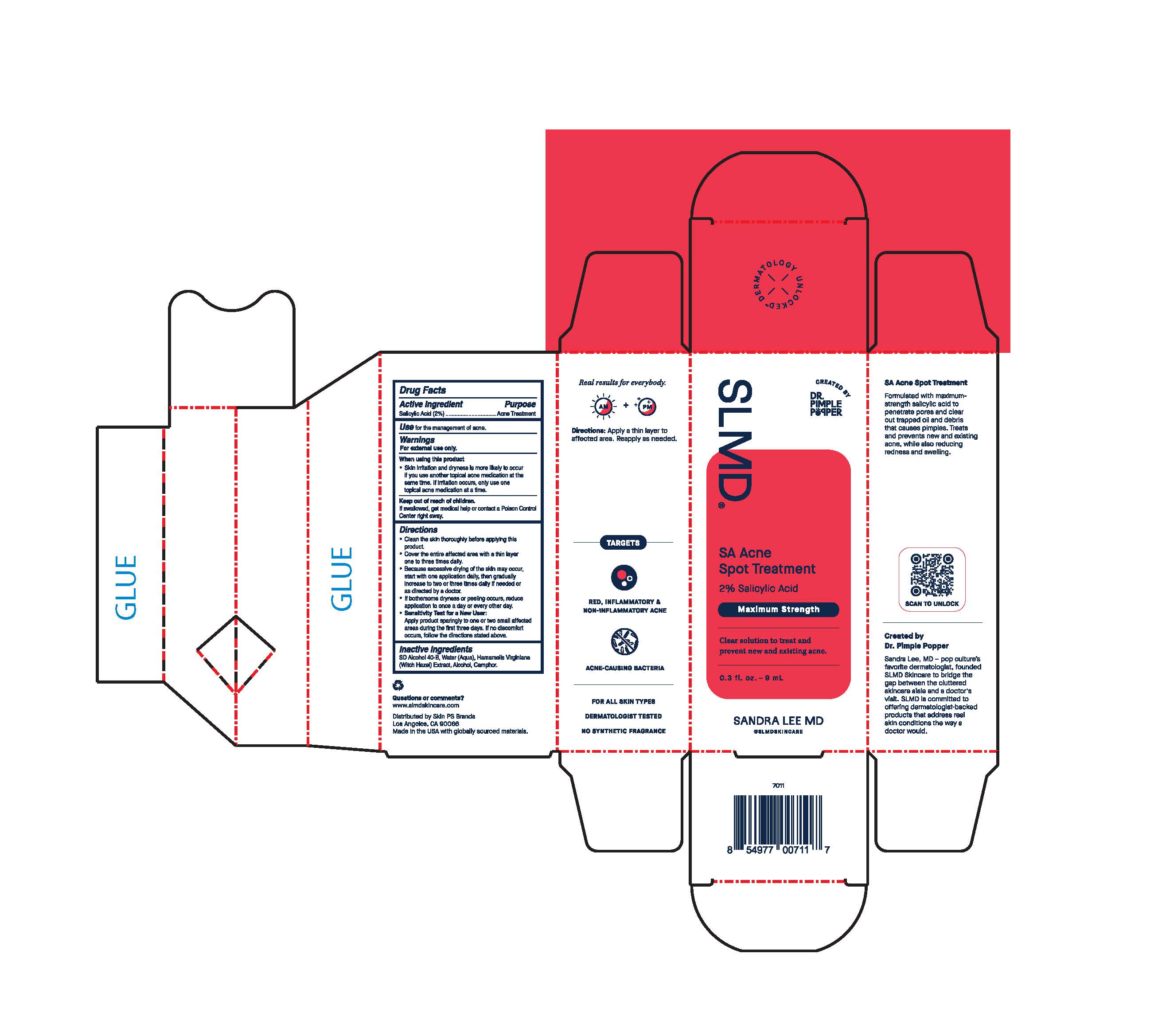 DRUG LABEL: SA Acne Spot Treatment
NDC: 73318-7003 | Form: LOTION
Manufacturer: Skin PS Brands
Category: otc | Type: HUMAN OTC DRUG LABEL
Date: 20251230

ACTIVE INGREDIENTS: SALICYLIC ACID 20 mg/1 g
INACTIVE INGREDIENTS: HAMAMELIS VIRGINIANA BARK; CAMPHOR (SYNTHETIC); WATER; ALCOHOL

SA Acne Spot Treatment

Active Ingredient

Salicylic Acid 2.0%

Purpose

Acne Treatment

Use

for the management of acne.

Warnings

For external use only.

When using this product

- Skin irritation and dryness is more likely to occur if you use another topical acne medication at the same time. If irritation occurs, only use one topical acne medication at a time.

Keep out of reach of children.

If swallowed, get medical help or contact a Poison Control Center right away.

Directions

- clean skin thoroughly before applying this product
- cover the entire affected area with a thin layer one to three times daily
- because excessive drying of the skin may occur, start with one application daily, then gradually increase to two or three daily if needed or as directed by a doctor
- if bothersome dryness or peeling occurs, reduce application to once a day or every other day
- Sensitivity Test for a New User:

Apply product sparingly to one or two small affected areas during the first 3 days. if no discomfort occurs, follow the directions stated above.

Inactive Ingredients

Alcohol Denat., Aqua/Water/Eau, Hamamelis Virginiana (Witch Hazel) Extract, Camphor.

Questions or comments?

www.slmdskincare.com

Distributed by Skin PS Brands

Los Angeles, CA 90066

Made in USA with globally sourced materials.

Real results for everybody.

AM + PM

Directions: Apply a thin layer to affected area. Reapply as needed.

TARGETS

RED, INFLAMMATORY & NON-INFLAMMATORY ACNE

ACNE CAUSING BACTERIA

FOR ALL SKIN TYPES

DERMATOLOGIST TESTED

NO SYNTHETIC FRAGRANCE

SA Acne Spot Treatment

Formulated with maximum-strength salicylic acid to penetrate pores and clear out trapped oil and debris to treat and prevent new and existing acne, while also reducing redness and swelling.

Created by Dr. Pimple Popper

Sandra Lee, MD - pop culture's favorite dermatologist, founded SLMD Skincare to bridge the gap between the cluttered skincare aisle and a doctor's visit. SLMD is committed to offering dermatologist-backed products that address real skin conditions the way a doctor would.

SLMD®

Created by Dr. Pimple Popper

SA Acne Spot Treatment

2% Salicylic Acid

Maximum Strength

Clear solution to treat and prevent new and existing acne.

0.3 fl. oz. - 9 mL

SANDRA LEE MD

@SLMDSKINCARE

Unit Carton: